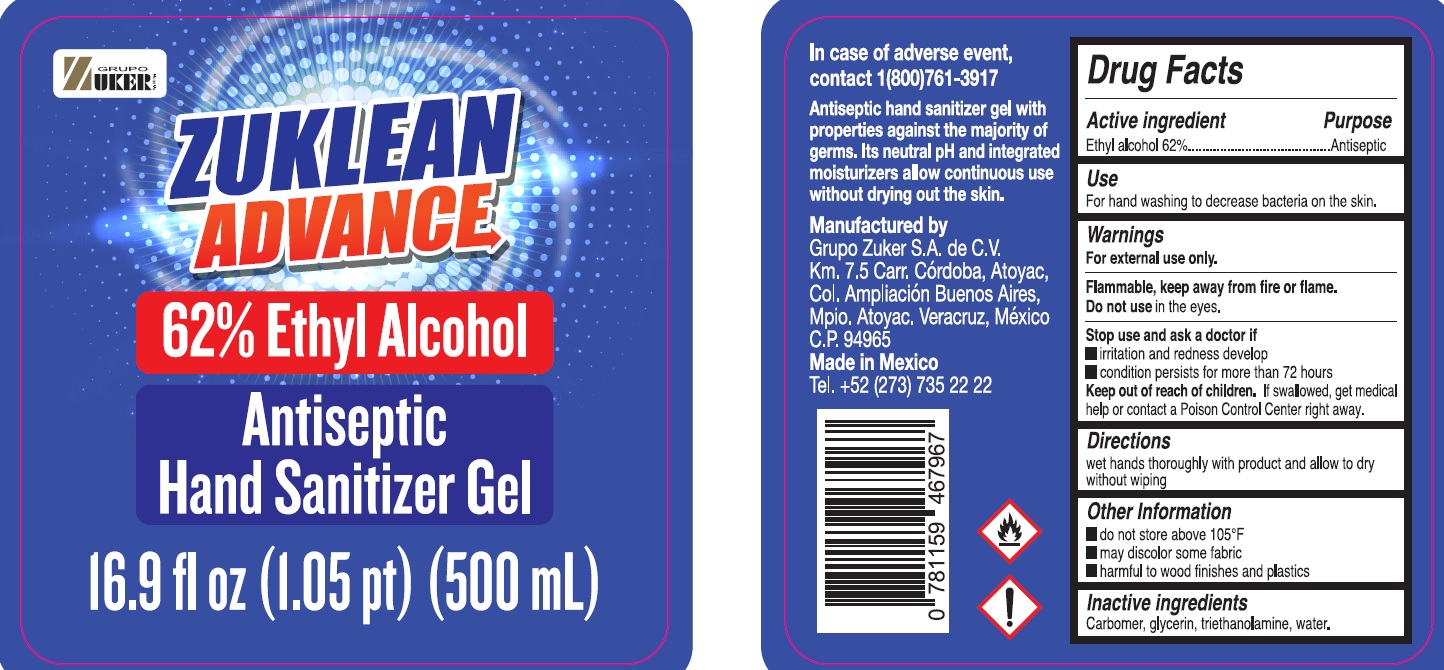 DRUG LABEL: Zuklean Advance 62 Ethyl Alcohol Hand Sanitizer GeL
NDC: 81814-001 | Form: GEL
Manufacturer: Grupo Zuker S.A. de C.V.
Category: otc | Type: HUMAN OTC DRUG LABEL
Date: 20210426

ACTIVE INGREDIENTS: ALCOHOL 62 mL/100 mL
INACTIVE INGREDIENTS: CARBOMER HOMOPOLYMER, UNSPECIFIED TYPE; GLYCERIN; TROLAMINE; WATER

Zuklean Advance 62 % Ethyl Alcohol Hand Sanitizer GeL

Active ingredient

Ethyl alcohol 62%

Purpose

Antiseptic

Use

For hand washing to decrease bacteria on the skin.

Warnings

For external use only. Flammable, keep away from fire or flame.

Do not use

in the eyes.

Stop use and ask a doctor if

- irritation and redness develop
- condition persists for more than 72 hours

Keep out of reach of children.

If swallowed, get medical help or contact a Poison Control Center right away.

Directions

wet hands thoroughly with product and allow to dry without wiping

Other Information

- do not store above 105°F
- may discolor some fabric
- harmful to wood finishes and plastics

Inactive ingredients

Carbomer, glycerin, triethanolamine, water.